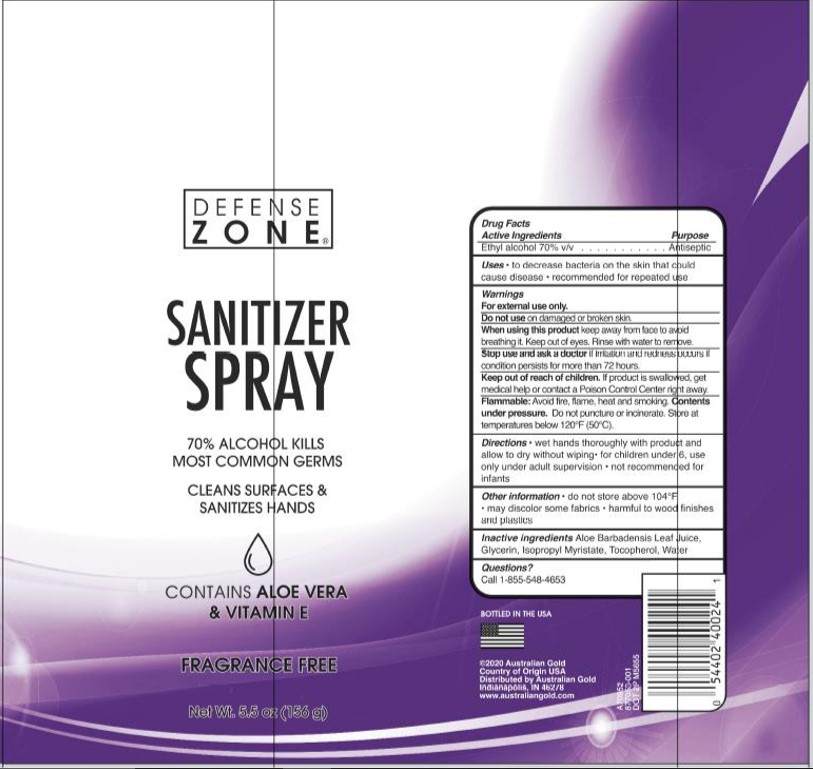 DRUG LABEL: Defense Zone
NDC: 13630-0161 | Form: SPRAY
Manufacturer: Prime Packaging
Category: otc | Type: HUMAN OTC DRUG LABEL
Date: 20200817

ACTIVE INGREDIENTS: ALCOHOL 0.7 mL/1 mL
INACTIVE INGREDIENTS: TOCOPHEROL; WATER; GLYCERIN; ISOPROPYL MYRISTATE; ALOE VERA LEAF

Defense Zone Sanitizer Spray

Active Ingredients

Ethyl Alcohol 70%

Purpose

Antiseptic

Uses

to decrease bacteria on the skin that could cause disease. recommrnded for repeated use

Warning

For external use only

Dot not use

Do not use on damaged or broken skin

When using this product

Keep away from face to avoid breathing it. Keep out of eyes. rinse with water to remove.

Stop use and ask a doctor

If irritation and redness occurs if condition persistes for more than 72 hours.

Keep out of reach of children

If product is swallowed, get medical help or contact a Posion Control Center right away.

Flammable

Avoid fire, flame, heat and smoking. Contents under pressre. do not punture or incinerate. Store at temperatures below 120°F(50°C).

Directions

wet hands thoroughly with product and allow to dry without wiping. for children under 6, use only under adult supervision. not recommended for infants.

Other Information

do not store above 104°F. may discolor some fabrics. harmful to wood finishes and plastics.

Inactive ingredients

Aloe Barbadensis Leaf Juice,Glycerin,Isopropyl Myristate, Tocopherol,Water.

Questions

Call 1 855-548-4653